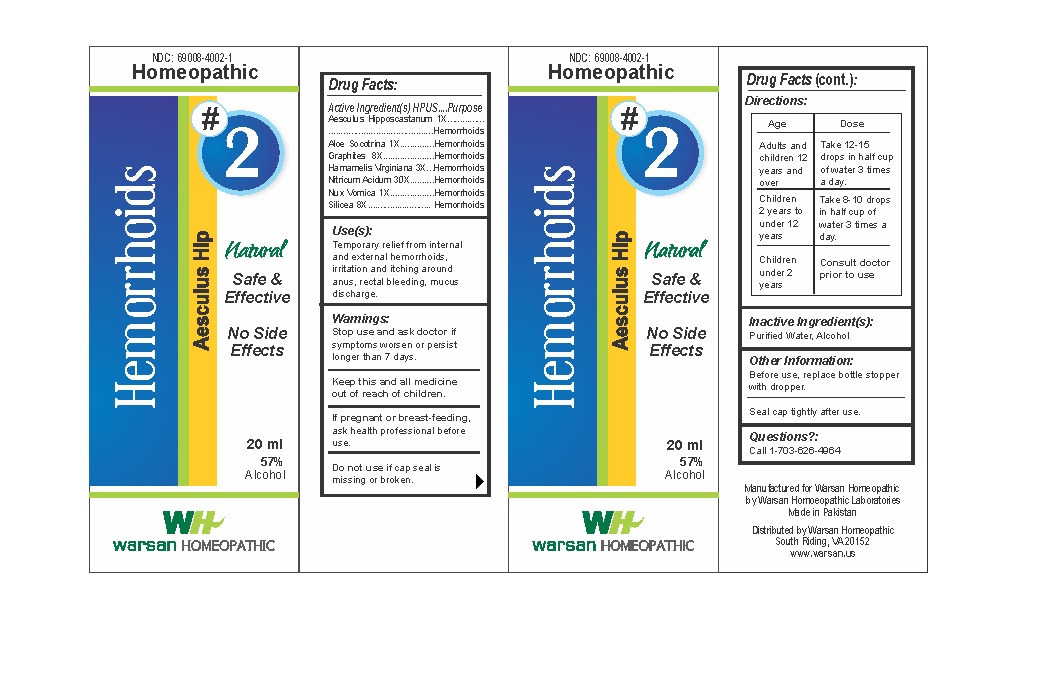 DRUG LABEL: Combination Remedy 2 - Hemorrhoids
NDC: 69008-4002 | Form: SOLUTION/ DROPS
Manufacturer: Warsan Homoeopathic Laboratories
Category: homeopathic | Type: HUMAN OTC DRUG LABEL
Date: 20171226

ACTIVE INGREDIENTS: GRAPHITE 8 [hp_X]/1 mL; HAMAMELIS VIRGINIANA ROOT BARK/STEM BARK 3 [hp_X]/1 mL; HORSE CHESTNUT 1 [hp_X]/1 mL; STRYCHNOS NUX-VOMICA SEED 1 [hp_X]/1 mL; SILICON DIOXIDE 8 [hp_X]/1 mL; ALOE VERA LEAF 1 [hp_X]/1 mL; NITRIC ACID 30 [hp_X]/1 mL
INACTIVE INGREDIENTS: ALCOHOL; WATER

Stop use and ask doctor if symptoms worsen or persist longer than 7 days.

If pregnant or breast-feeding, ask health professional before use.

Do not use if tamper evident seal is missing or broken.

Keep out of reach of children.

ACTIVE INGREDIENT

Aesculus Hipposcastanum 1X

Aloe Socotrina 1X

Graphites 8X

Hamamelis Virginiana 3X

Nitricum Acidum 30X

Nux Vomica 1X

Silicea 8X

PURPOSE

Temporary relief from internal and external hemorrhoids, irritation and itching around anus, rectal bleeding, mucus discharge.

INACTIVE INGREDIENT

Purified Water

Alcohol

DOSAGE AND ADMINISTRATION

Adults and children 12 years and older: Take 10-15 drops in half cup of water 3 times a day.

Children 2 years to under 12 years: Take 8-10 drops in half cup of water of 3 times a day.

Children under 2 years: Consult doctor prior to use.

INDICATIONS AND USAGE

Temporary relief from internal and external hemorrhoids, irritation and itching around anus, rectal bleeding, mucus discharge.